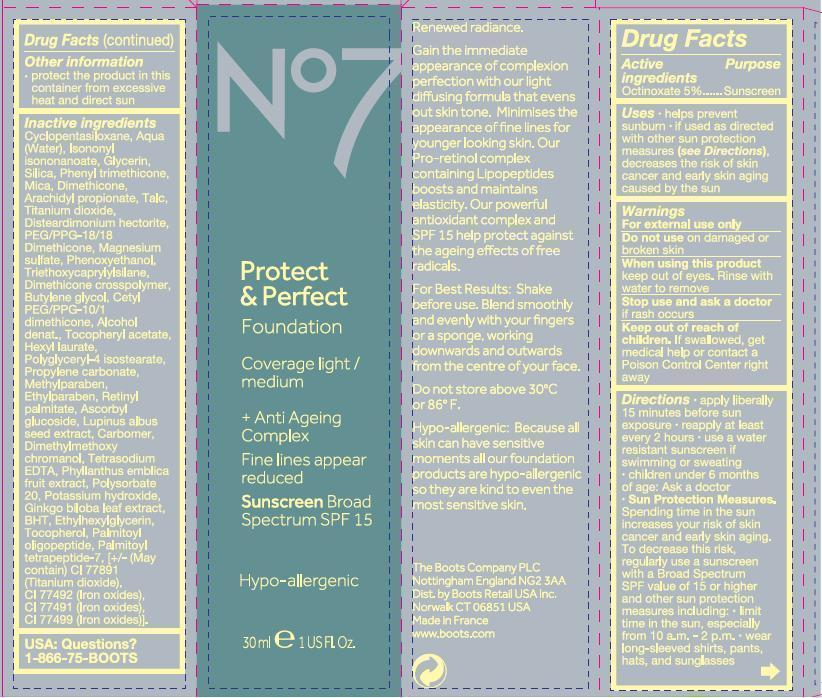 DRUG LABEL: No7 Protect and Perfect Foundation Sunscreen Broad Spectrum SPF 15 Cool Beige
NDC: 61589-5312 | Form: EMULSION
Manufacturer: BCM Cosmetique SAS
Category: otc | Type: HUMAN OTC DRUG LABEL
Date: 20121030

ACTIVE INGREDIENTS: OCTINOXATE 1.5 g/30 g
INACTIVE INGREDIENTS: CYCLOMETHICONE 5; WATER; ISONONYL ISONONANOATE; GLYCERIN; SILICON; PHENYL TRIMETHICONE; MICA; DIMETHICONE; ARACHIDYL PROPIONATE; TALC; TITANIUM DIOXIDE; PEG/PPG-18/18 DIMETHICONE; MAGNESIUM SULFATE; PHENOXYETHANOL; TRIETHOXYCAPRYLYLSILANE; BUTYLENE GLYCOL; CETYL PEG/PPG-10/1 DIMETHICONE (HLB 1.5); .ALPHA.-TOCOPHEROL ACETATE; HEXYL LAURATE; POLYGLYCERYL-4 ISOSTEARATE; PROPYLENE CARBONATE; METHYLPARABEN; ETHYLPARABEN; VITAMIN A PALMITATE; ASCORBYL GLUCOSIDE; LUPINUS ALBUS SEED; CARBOMER HOMOPOLYMER TYPE C; EDETATE SODIUM TETRAHYDRATE; PHYLLANTHUS EMBLICA FRUIT JUICE; POLYSORBATE 20; POTASSIUM HYDROXIDE; GINKGO BILOBA LEAF OIL; BUTYLATED HYDROXYTOLUENE; TOCOPHEROL; PALMITOYL OLIGOPEPTIDE; PALMITOYL TETRAPEPTIDE-7; TITANIUM DIOXIDE; FERRIC OXIDE YELLOW; FERRIC OXIDE RED; FERROSOFERRIC OXIDE

Carton active ingredient section

Active ingredients Octinoxate 5%

Purpose sunscreen.

Uses

Uses - helps prevent sunburn.
if used with as directed with other sun protection measures (see Directions) decreases the risk of skin cancer and early skin aging caused by the sun

Warnings

For external use only

Do not use on damaged or broken skin

When using this product keep out of eyes. Rinse with water to remove

Ask a doctor

Stop use and ask a doctor if rash occurs.

Keep out of reach of children. If swallowed, get medical help or contact a Poison Centre right away.

Directions

apply liberally 15 minutes bfore sun exposure

reapply at least every 2 hours.

use a water resistant sunscreen if swimming or sweating.

children under 6 months of age: Ask a doctor.

Sun Protection Measures.

Spending time in the sun increases your risk of skin cancer and early skin aging. To decrease this risk, regularly use a sunscreen with a Broad Spectrum SPF value of 15 or higher and other sun protection measures including:

limit time in the sun, especially from 10 a.m.–2 p.m.

wear long-sleeved shirts, pants, hats, and sunglasses

Storage

Other information - protect the product in this container from excessive heat and direct sun

Inactive ingredients

Cyclopentasiloxane, Aqua (Water) Isononyl isononanoate, Glycerin, Silica, Pheny trimethicone, Mica, Dimethicone, Arachidyl propionate, Talc, Titanium dioxide, Disteardimonium hectorite, PEG/PPG-10/1 dimethicone, Alcohol denat., Tocopheryl acetate, Hexyl laurate, Polyglyceryl-4 isostearate, Propylene carbonate, Methylparaben, Ethylparaben, Retinyl palmitate, Ascorbyl glucoside, Lupinus albus seed extract, Carbomer, Dimethylmethoxychromanol, Tetasodium EDTA, Phyllanthus emblica fruit extract, Polysorbate 20, Potasium hyroxide, Ginkgo biloba leaf extract, BHT, Ethylhexylglycerin, Tocopherol, Palmitoyl oligopeptide, Palmitoyl Tetrapeptide-7. May contain CI 77891 (Titanium dioxide), CI 77492 (Iron oxides), CI 77491 (Iron oxides), CI 77499 (Iron oxides).

Description

Renewed radiance.

Gain the immediate appearance of complexion perfection with our light diffusing formula that evens out skin tone. Minimises the appearance of fine lines for younger looking skin. Our Pro-retinol complex containing Lipopeptides boosts and maintain elasticity. Our powerful antioxidant complex and SPF 15 help protect against the ageing effects of free radicals.

For Best Results: Shake before use. Blend smoothly and evenly with your fingers or a sponge, working downwards and outwards from the centre of your face.

Do not store above 30 degrees C or 86 degrees F.

Hypo-allergenic: Because all skin can have sensitive moments all our foundation products are hypo-allergenic so they are kind to even the most sensitive skin.

INFORMATION

The Boots Company PLC

Nottingham

England

NG3 3AA

Dist by Boots Retail USA Inc Norwalk CT 06851 USA

Made in France

www.boots.com.

Bottle label

No7 Protect and Perfect Foundation Sunscreen Broad Spectrum SPF 15

Younger looking skin

Hypo-allergenic 30ml 1 US Fl Oz

Active ingredients

Octinoxate 5%.

Warnings

Avoid contact with eyes. If product gets into the eyes, rinse well with water immediately.

Description

Smoothes and moisturises for younger looking skin and a flawless, radiant complexion.

For Best Results: Shake before use. Blend on smoothly and evenly with your fingers or a sponge.

PATIENT COUNSELING INFORMATION

The Boots Company PLC Nottingham England NG2 3AA

Dist by Boots Retail USA InC Norwalk CT 06851 USA

Made in France

www.boots.com.

carton label

carton label1